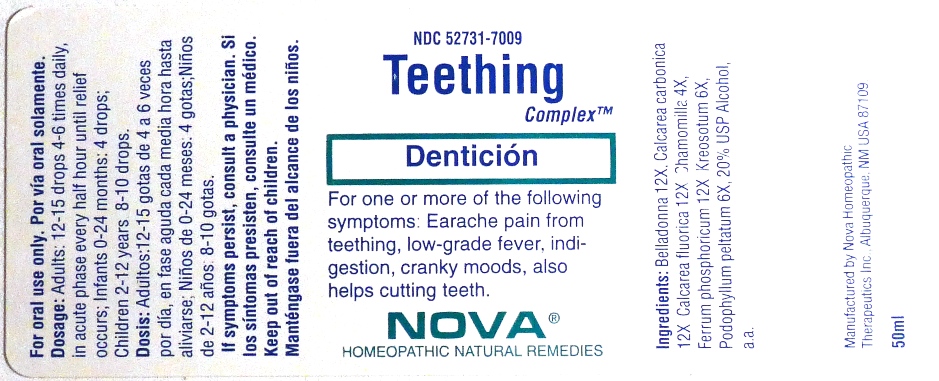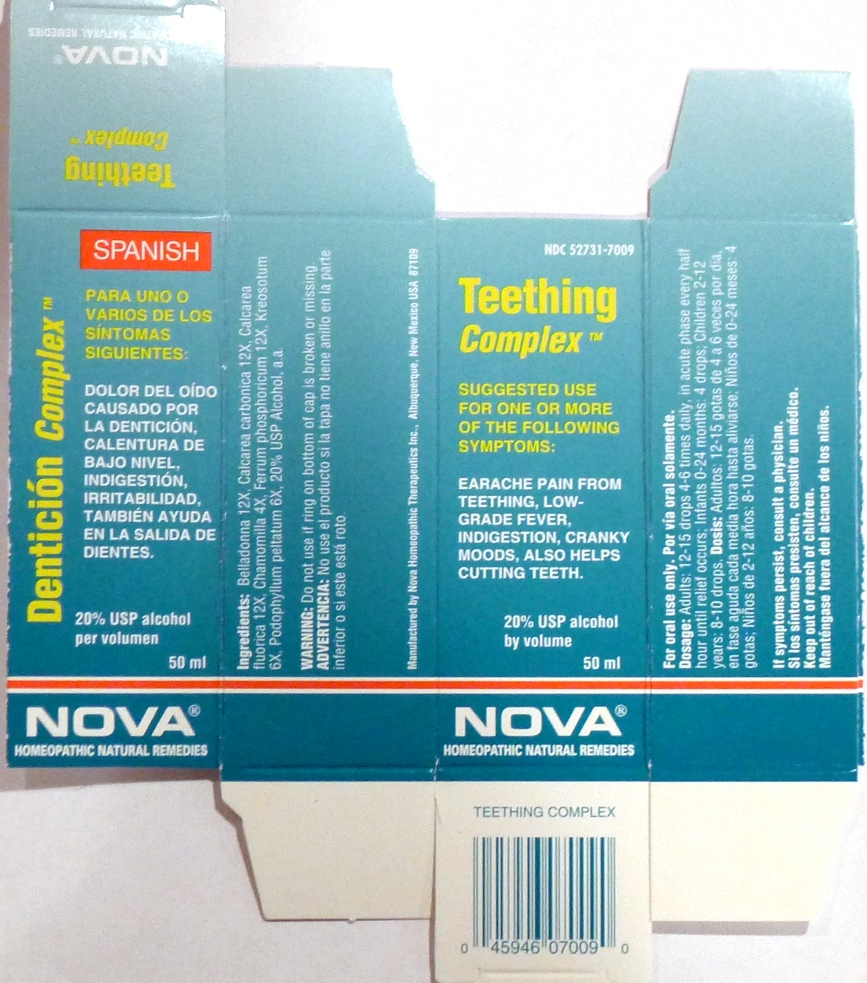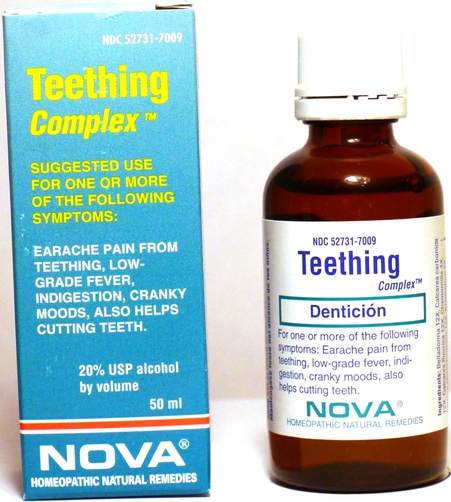 DRUG LABEL: Teething Complex
NDC: 52731-7009 | Form: LIQUID
Manufacturer: Nova Homeopathic Therapeutics, Inc.
Category: homeopathic | Type: HUMAN OTC DRUG LABEL
Date: 20110601

ACTIVE INGREDIENTS: ATROPA BELLADONNA 12 [hp_X]/1 mL; OYSTER SHELL CALCIUM CARBONATE, CRUDE 12 [hp_X]/1 mL; CALCIUM FLUORIDE 12 [hp_X]/1 mL; MATRICARIA RECUTITA 4 [hp_X]/1 mL; FERRUM PHOSPHORICUM 12 [hp_X]/1 mL; WOOD CREOSOTE 6 [hp_X]/1 mL; PODOPHYLLUM 6 [hp_X]/1 mL
INACTIVE INGREDIENTS: ALCOHOL

Teething Complex

Purpose:

Suggested use for one or more of the following symptoms:
Earache pain from teething, low-grade fever, indigestion, cranky moods, also helps cutting teeth.

Usage and Dosage:

For oral use only.

DOSAGE AND ADMINISTRATION

Adults:
In Acute Phase:
12-15 drops, every half hour until relief occurs
When Relief Occurs:
12-15 drops, 4-6 times per day
Children 2-12 years:
8-10 drops, 4-6 times per day
Infants 0-24 months:
4 drops, 4-6 times per day

Warnings:

Keep out of reach of children.

WARNINGS

If symptoms persist, consult a physician.
Do not use if ring on bottom of cap is broken or missing.

Active Ingredients:

Belladonna 12X, Calcarea carbonica 12X, Calcarea fluorica 12X, Chamomilla 4X, Ferrum phosphoricum 12X, Kreosotum 6X, Podophyllum peltatum 6X

Inactive Ingredients:

Alcohol, 20% USP

QUESTIONS

Manufactured by Nova Homeopathic Therapeutics Inc., Albuquerque, New Mexico USA 87109
1-800-225-8094

PACKAGE LABEL

Teething Complex Product

Teething Complex Bottle Label

Teething Complex Box